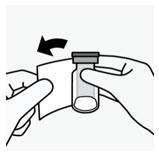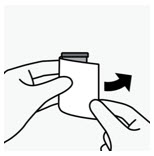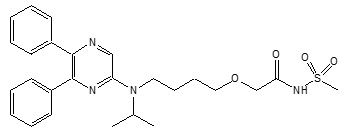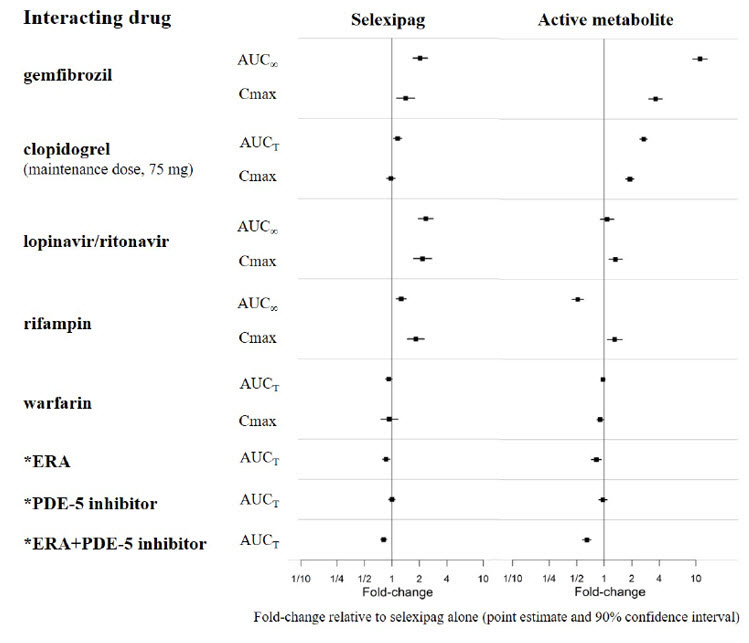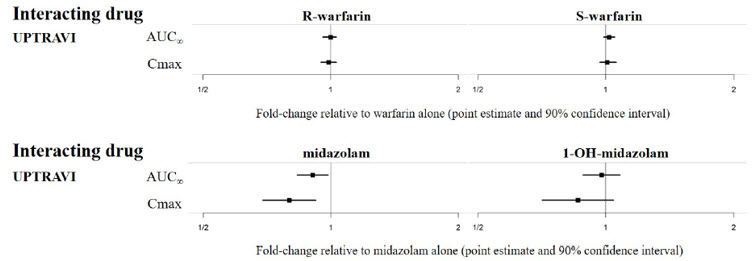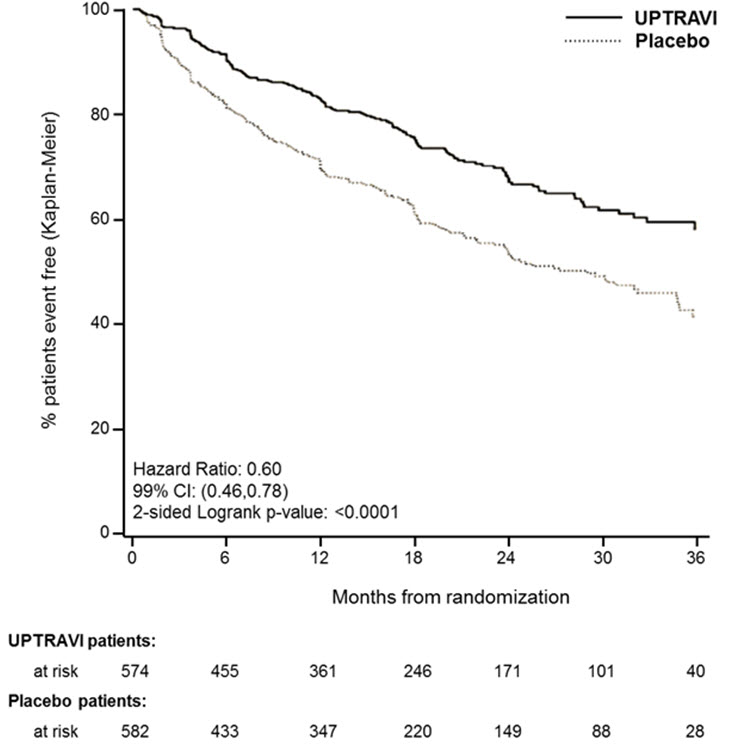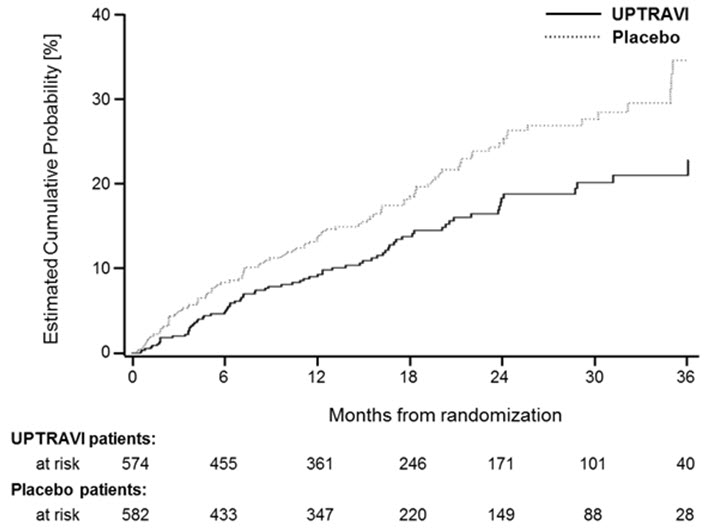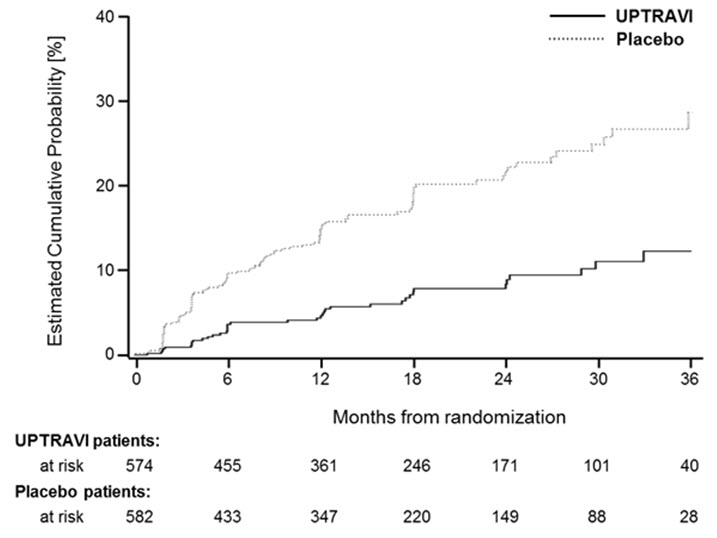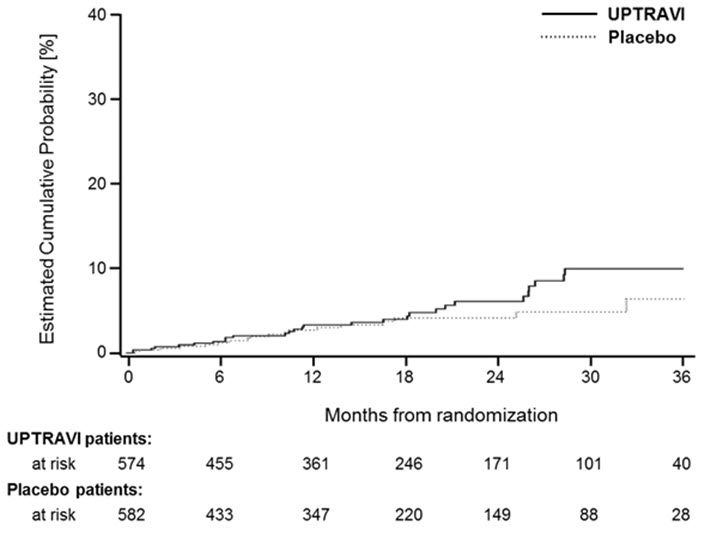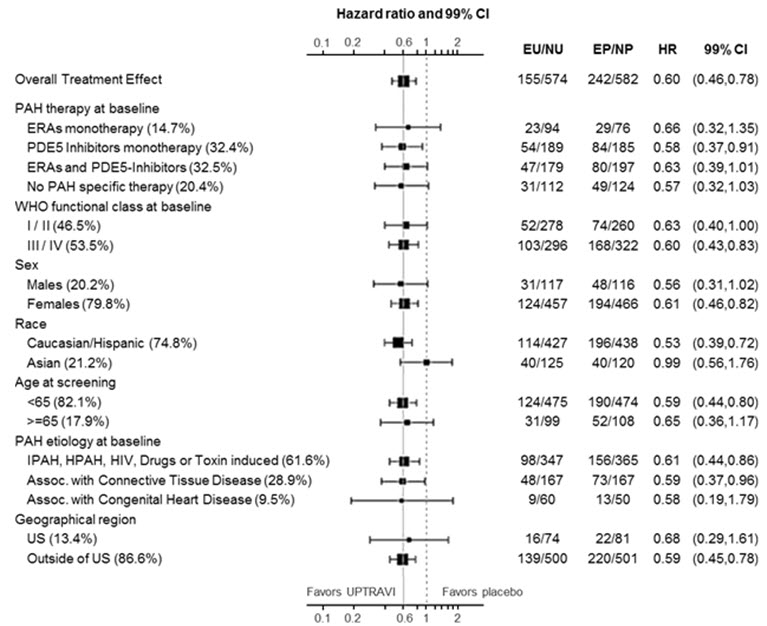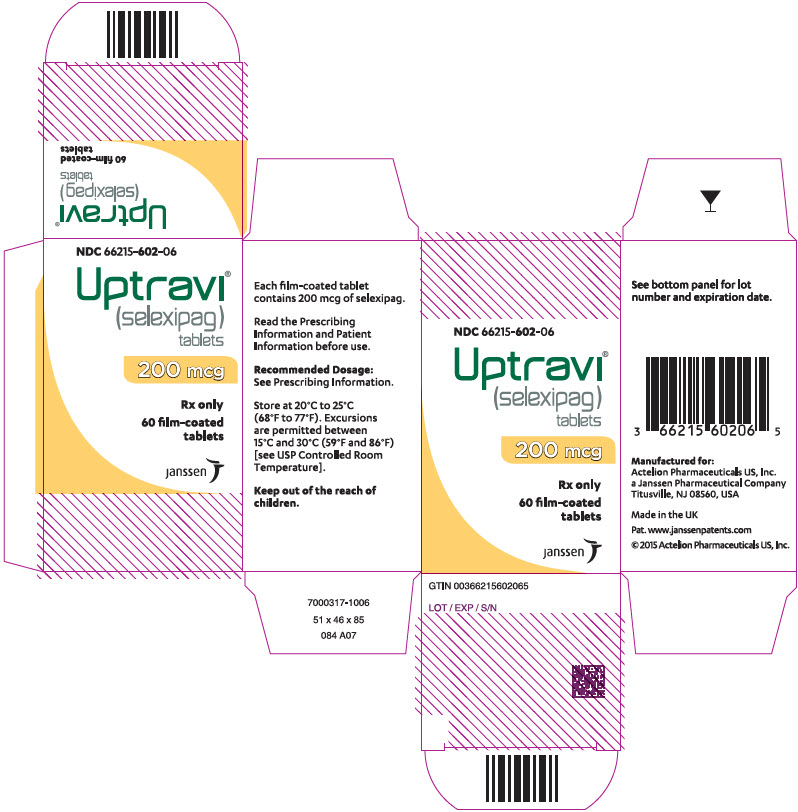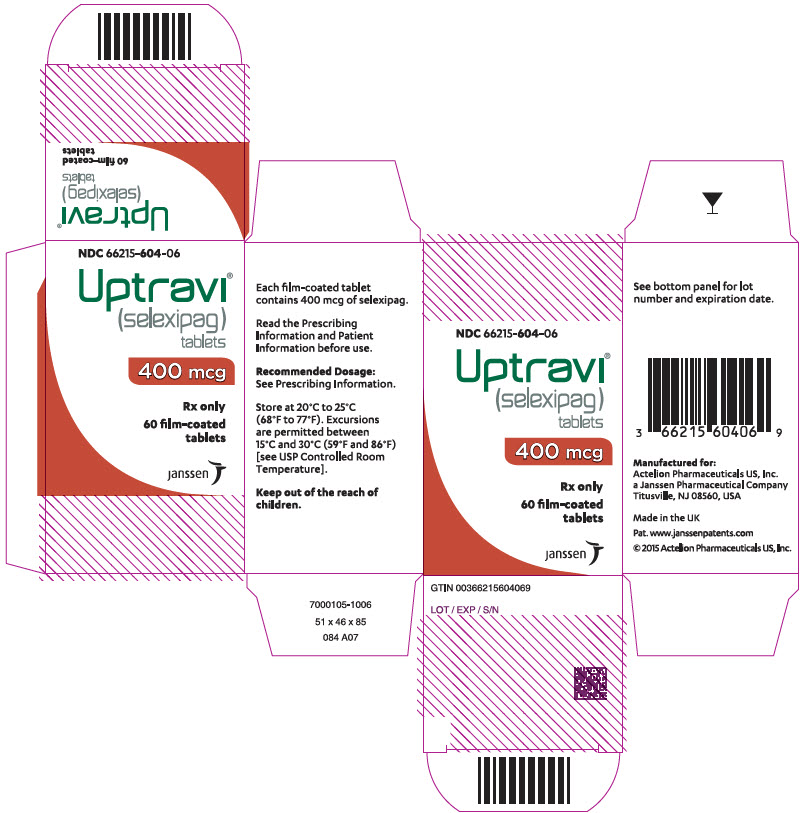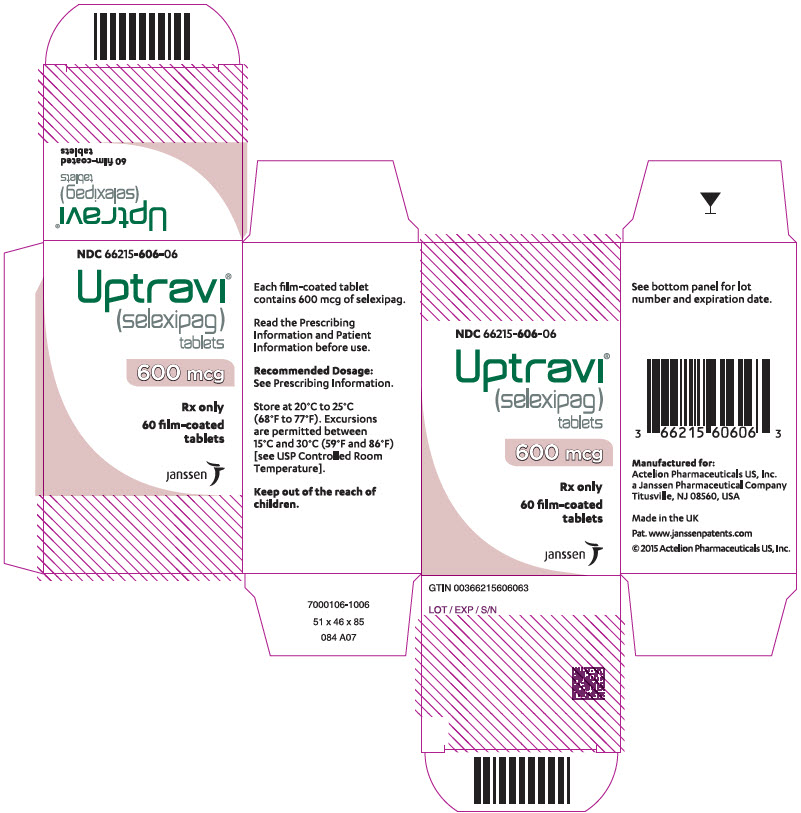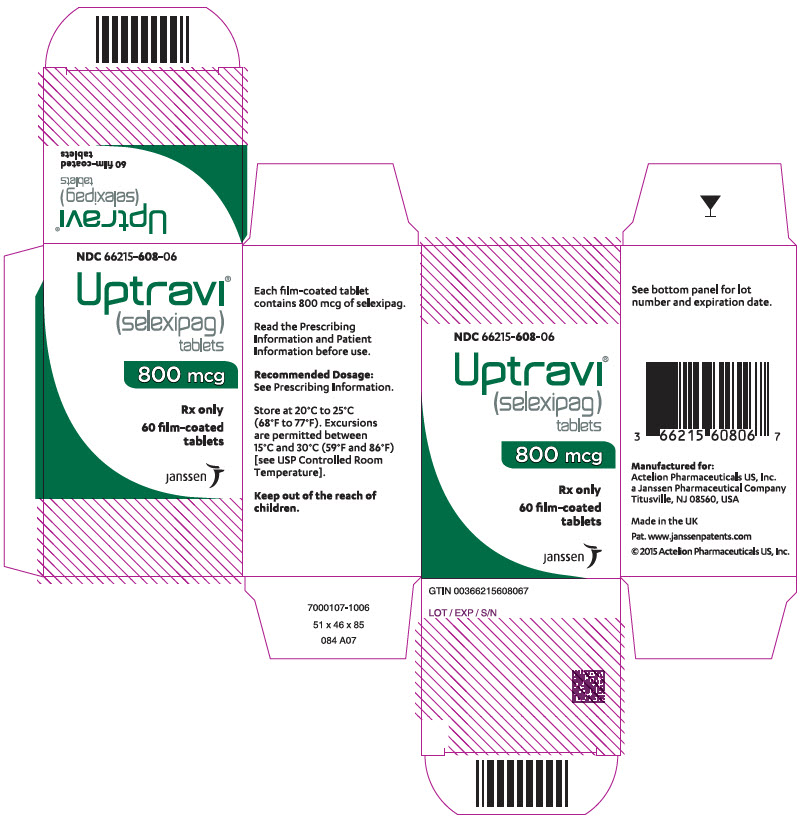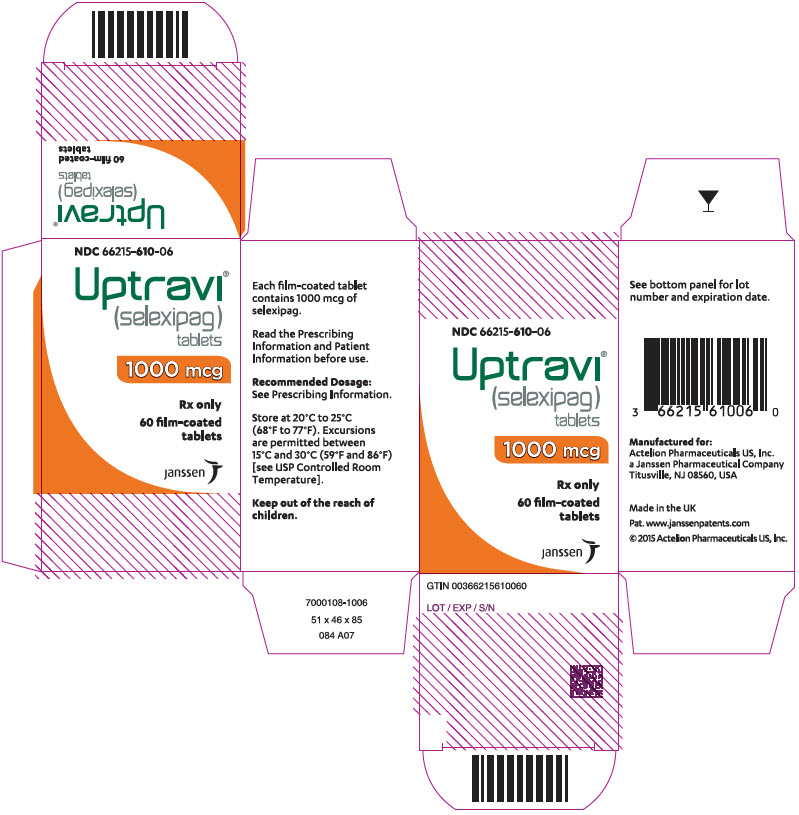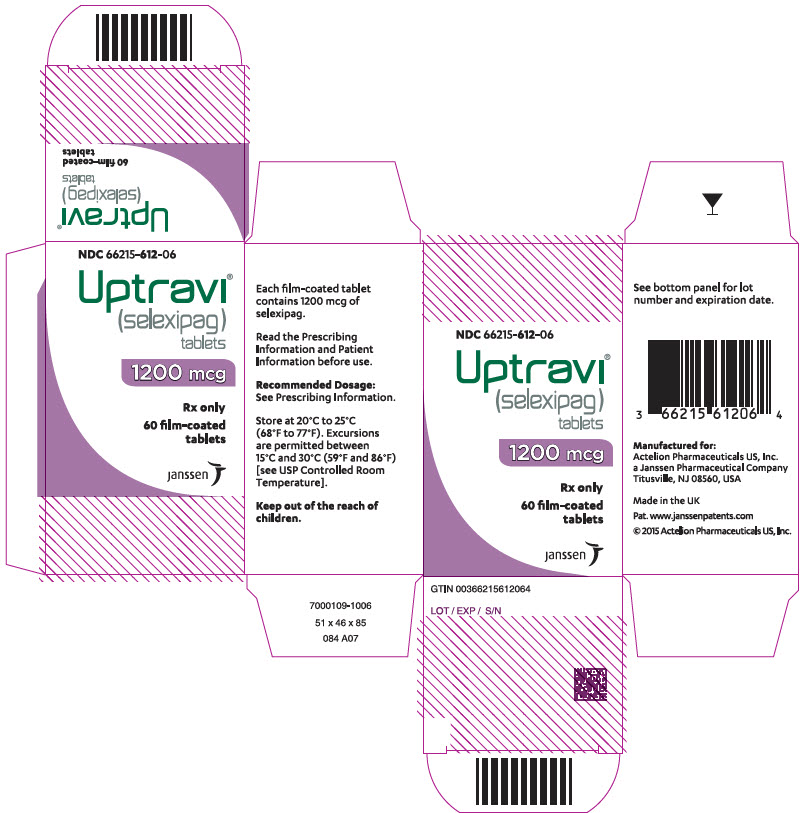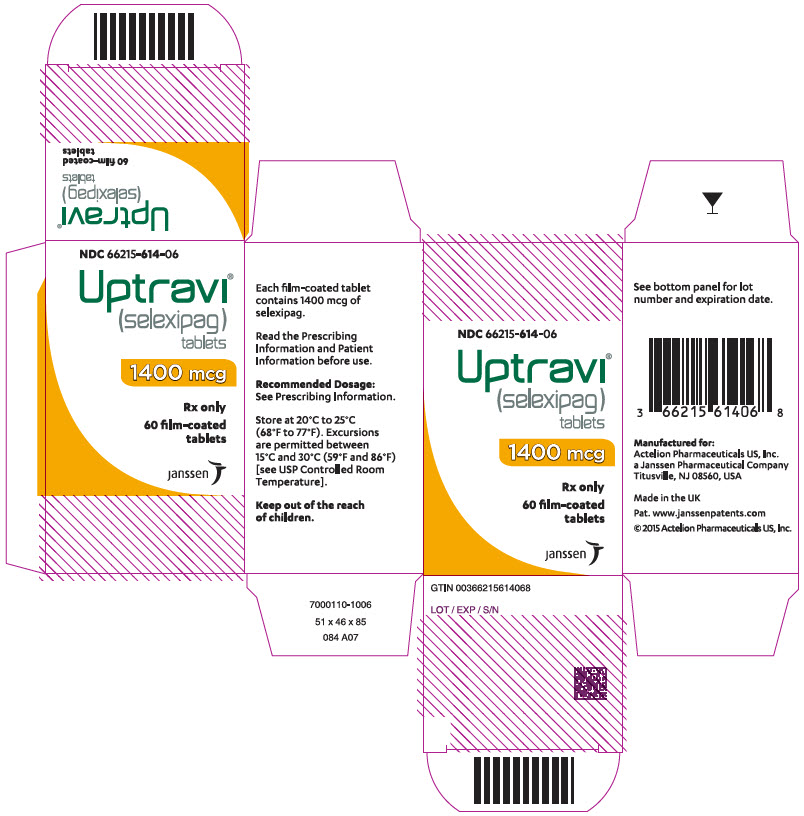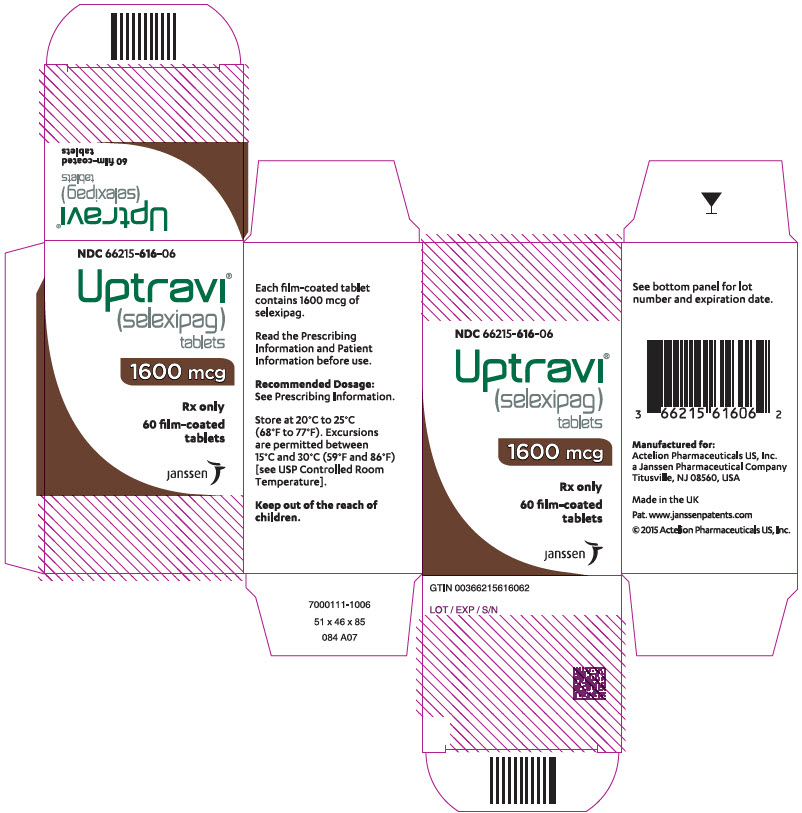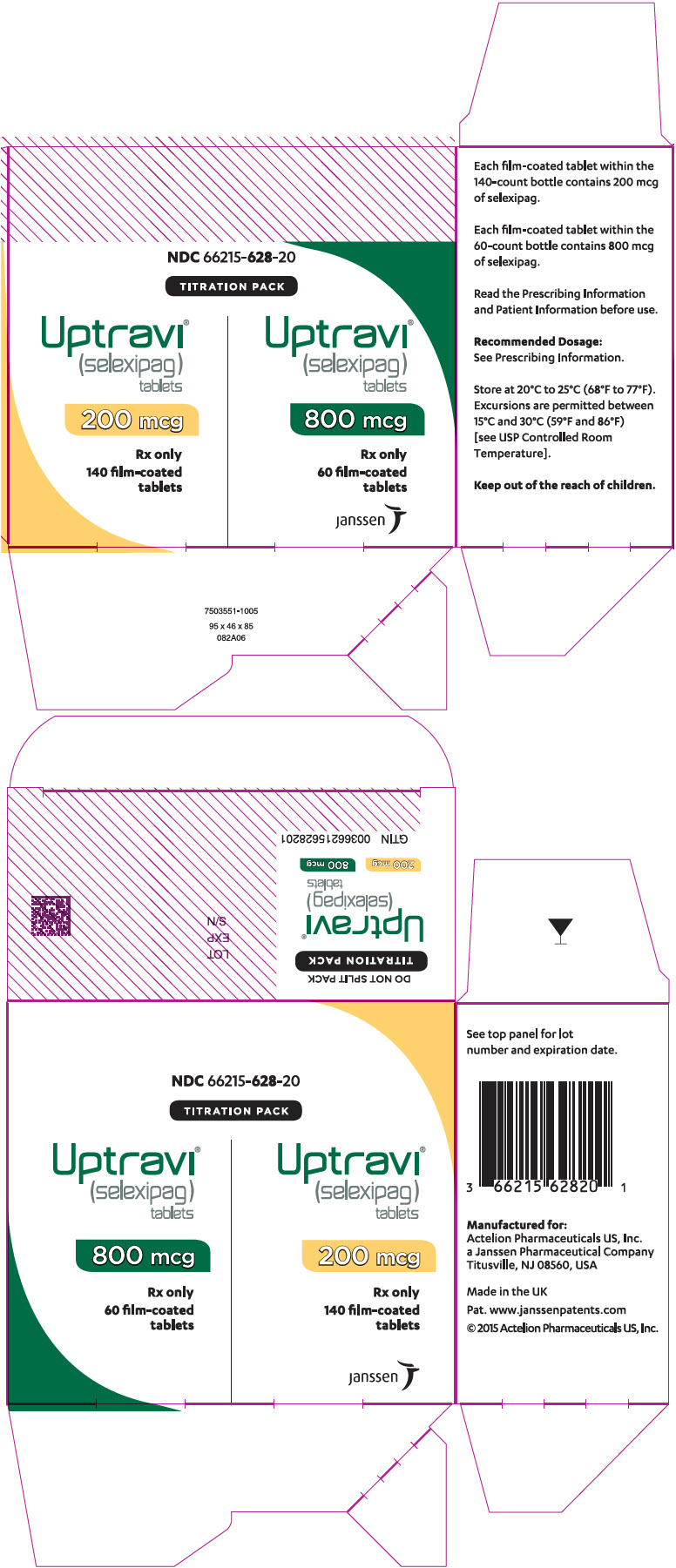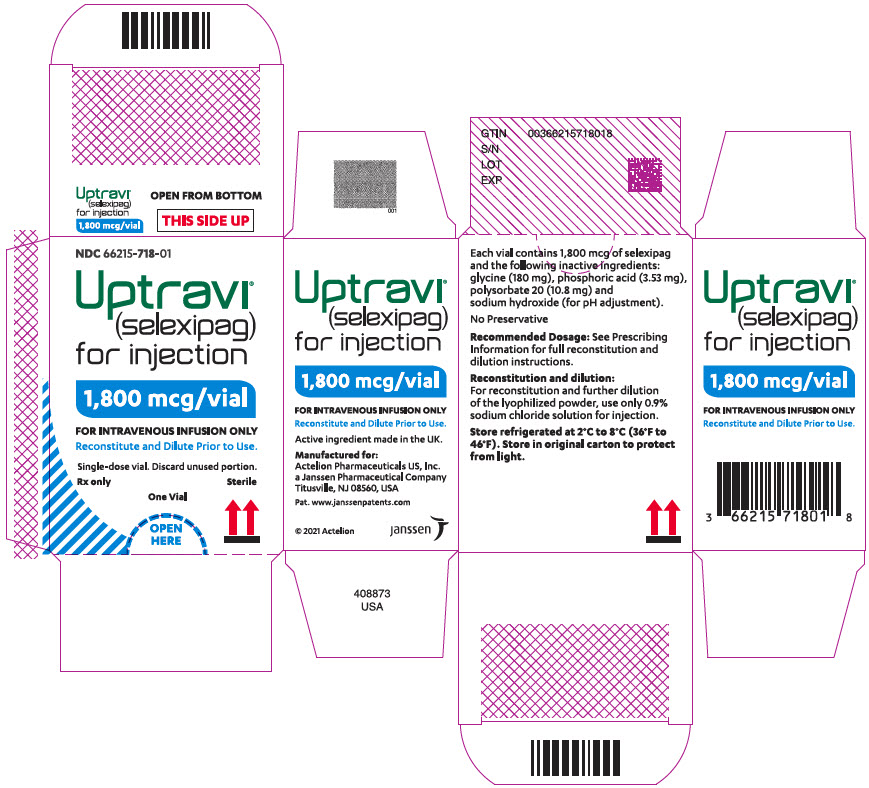 DRUG LABEL: UPTRAVI
NDC: 66215-602 | Form: TABLET, COATED
Manufacturer: Actelion Pharmaceuticals US, Inc.
Category: prescription | Type: HUMAN PRESCRIPTION DRUG LABEL
Date: 20240708

ACTIVE INGREDIENTS: SELEXIPAG 200 ug/1 1
INACTIVE INGREDIENTS: MANNITOL; STARCH, CORN; LOW-SUBSTITUTED HYDROXYPROPYL CELLULOSE, UNSPECIFIED; MAGNESIUM STEARATE; HYPROMELLOSE, UNSPECIFIED; HYDROXYPROPYL CELLULOSE (1200000 WAMW); PROPYLENE GLYCOL; TITANIUM DIOXIDE; FERRIC OXIDE YELLOW; CARNAUBA WAX

HIGHLIGHTS OF PRESCRIBING INFORMATION

These highlights do not include all the information needed to use UPTRAVI safely and effectively. See full prescribing information for UPTRAVI.
UPTRAVI® (selexipag) tablets, for oral use
UPTRAVI® (selexipag) for injection, for intravenous use
Initial U.S. Approval: 2015

RECENT MAJOR CHANGES

Contraindications (4) | 10/2021

1 INDICATIONS AND USAGE

- UPTRAVI is a prostacyclin receptor agonist indicated for the treatment of pulmonary arterial hypertension (PAH, WHO Group I) to delay disease progression and reduce the risk of hospitalization for PAH. (1.1)

2 DOSAGE AND ADMINISTRATION

- UPTRAVI tablets starting dose: 200 mcg twice daily. (2.1)
- Increase the dose by 200 mcg twice daily at weekly intervals to the highest tolerated dose up to 1600 mcg twice daily. (2.1)
- Maintenance dose is determined by tolerability. (2.1)
- Moderate hepatic impairment: Starting dose 200 mcg once daily, increase the dose by 200 mcg once daily at weekly intervals to the highest tolerated dose up to 1600 mcg. (2.5)
- UPTRAVI for injection dose is determined by the patient's current dose of UPTRAVI tablets. Administer UPTRAVI for injection by intravenous infusion, twice daily. (2.2)

See Full Prescribing Information for instructions on preparation and administration. (2.3).

3 DOSAGE FORMS AND STRENGTHS

- Tablets: 200 mcg, 400 mcg, 600 mcg, 800 mcg, 1000 mcg, 1200 mcg, 1400 mcg, 1600 mcg. (3)
- For Injection: 1800 mcg of selexipag as a lyophilized powder in a single-dose vial for reconstitution and dilution. (3)

4 CONTRAINDICATIONS

Concomitant use with strong CYP2C8 inhibitors. (4, 7.1, 12.3)

Hypersensitivity to the active substance or to any of the excipients. (4)

5 WARNINGS AND PRECAUTIONS

Pulmonary edema in patients with pulmonary veno-occlusive disease. If confirmed, discontinue treatment. (5.1)

6 ADVERSE REACTIONS

Adverse reactions occurring more frequently (≥5%) on UPTRAVI compared to placebo are headache, diarrhea, jaw pain, nausea, myalgia, vomiting, pain in extremity, and flushing. (6.1)

To report SUSPECTED ADVERSE REACTIONS, contact Janssen at 1-800-526-7736 (1-800-JANSSEN) or FDA at 1-800-FDA-1088 or www.fda.gov/medwatch.

7 DRUG INTERACTIONS

- Moderate CYP2C8 inhibitors (e.g., clopidogrel, deferasirox and teriflunomide) increase exposure to the active metabolite of UPTRAVI. Reduce the dosing of UPTRAVI to once daily (2.6, 7.1, 12.3).
- CYP2C8 inducers (e.g., rifampin) decrease exposure to the active metabolite. Increase up to twice the dose of UPTRAVI (7.2, 12.3)

8 USE IN SPECIFIC POPULATIONS

- Nursing mothers: Discontinue UPTRAVI or breastfeeding. (8.2)
- Severe hepatic impairment: Avoid use. (8.6)

FULL PRESCRIBING INFORMATION

1 INDICATIONS AND USAGE

1.1 Pulmonary Arterial Hypertension

UPTRAVI is indicated for the treatment of pulmonary arterial hypertension (PAH, WHO Group I) to delay disease progression and reduce the risk of hospitalization for PAH.

Effectiveness of UPTRAVI tablets was established in a long-term study in PAH patients with WHO Functional Class II–III symptoms.

Patients had idiopathic and heritable PAH (58%), PAH associated with connective tissue disease (29%), PAH associated with congenital heart disease with repaired shunts (10%) [see Clinical Studies (14.1)] .

2 DOSAGE AND ADMINISTRATION

2.1 Recommended Dosage

UPTRAVI Film-coated Tablets

The recommended starting dosage of UPTRAVI tablets is 200 micrograms (mcg) given twice daily. Tolerability may be improved when taken with food [see Clinical Pharmacology (12.3)] .

Increase the dose in increments of 200 mcg twice daily, usually at weekly intervals, to the highest tolerated dose up to

1600 mcg twice daily. If a patient reaches a dose that cannot be tolerated, the dose should be reduced to the previous tolerated dose.

Do not split, crush, or chew tablets.

UPTRAVI for Injection

Use UPTRAVI for injection in patients who are temporarily unable to take oral therapy.

Administer UPTRAVI for injection twice daily by intravenous infusion at a dose that corresponds to the patient's current dose of UPTRAVI tablets (see Table 1). Administer UPTRAVI for injection as an 80-minute intravenous infusion.

2.2 Preparation Instructions

Reconstitute and further dilute UPTRAVI for injection prior to intravenous infusion following aseptic procedures.

Determine the dose and total volume of reconstituted UPTRAVI solution required (see Table 1).

Reconstitution

- Remove the carton of UPTRAVI for injection from the refrigerator and allow to stand for approximately 30 to 60 minutes to reach room temperature (20°C to 25°C [68°F to 77°F]).
- The vial needs to be protected from light at all times. Ensure the protective wrap around label is covering the entire vial.
- Peel back light protective wrap on vial to inspect the contents in the vial. It should appear white to almost white broken cake or powdered material. Immediately close the light protective wrap on the vial.
- Reconstitute UPTRAVI for injection using a polypropylene syringe with 8.6 mL of 0.9% Sodium Chloride Injection, USP and slowly inject into the UPTRAVI vial with the stream directed toward the inside wall of the vial to obtain a concentration of 225 mcg/mL of selexipag.
- Document date and time of first puncture. Complete infusion within 4 hours of first puncture.
- Gently invert the vial and repeat until powder is completely dissolved. Do not shake.
- Inspect the vial by peeling back the light protective wrap around label for discoloration. The reconstituted solution should appear clear, colorless and free from foreign material. Do not use if the reconstituted solution is discolored, cloudy, or contains visible particles.

Dilution

- UPTRAVI for injection must be diluted in glass containers only.
- Withdraw 100 mL of 0.9% Sodium Chloride Injection, USP and transfer into an empty sterile glass container.
- Withdraw the required volume of reconstituted solution (see Table 1 for reconstituted transfer volume) from the UPTRAVI vial using a single, appropriately sized polypropylene syringe and dilute into the glass container containing 100 mL 0.9% Sodium Chloride Injection, USP to obtain the desired final dose.
- Mix the diluted UPTRAVI infusion solution by gentle inversion of the glass container 5 times. Do not shake.
- Protect diluted UPTRAVI infusion solution from light at all times. Assign a 4-hour expiry from the time of first vial puncture and wrap the glass container completely with light protective cover.
- The UPTRAVI infusion solution should be kept at room temperature (20°C–25°C [68°F–77°F]) and must be infused within 4 hours from the first puncture of the vial stopper (including infusion time).
- Parenteral drug products should be inspected visually for particulate matter and discoloration prior to administration. The diluted UPTRAVI infusion solution should be clear and colorless. Discard if particulate matter is observed.

UPTRAVI for injection vials are single-dose, for single administration. All remaining reconstituted product must be discarded.

Table 1 Dosing Table for UPTRAVI intravenous based on current UPTRAVI tablets dose
UPTRAVI tablets dose (mcg) for twice daily dosing | Corresponding IV UPTRAVI Dose (mcg) for twice daily dosing | Reconstituted transfer volume (mL) for dilution
200 | 225 | 1.0
400 | 450 | 2.0
600 | 675 | 3.0
800 | 900 | 4.0
1000 | 1125 | 5.0
1200 | 1350 | 6.0
1400 | 1575 | 7.0
1600 | 1800 | 8.0

2.3 Administration Instructions

Administer by intravenous infusion over 80 minutes using an infusion set made of DEHP-free polyvinyl chloride (PVC), natural latex rubber-free microbore tubing protected from light.

Do not use a filter for administration.

Once the solution for infusion glass container is empty, continue the infusion at the same rate with 0.9% saline to empty the remaining solution for infusion in the IV line, to ensure that the entire solution for infusion has been administered.

2.4 Interruptions and Discontinuations

If a dose of UPTRAVI is missed, patients should take a missed dose as soon as possible unless the next dose is within the next 6 hours.

If treatment is missed for 3 days or more, restart UPTRAVI at a lower dose and then retitrate.

2.5 Dosage Adjustment in Patients with Hepatic Impairment

No dose adjustment of UPTRAVI is necessary for patients with mild hepatic impairment (Child-Pugh class A).

For patients with moderate hepatic impairment (Child-Pugh class B), the starting dose of UPTRAVI tablets is 200 mcg once daily. Increase in increments of 200 mcg once daily at weekly intervals, as tolerated [see Use in Specific Populations (8.6) and Clinical Pharmacology (12.3)] .

Avoid use of UPTRAVI in patients with severe hepatic impairment (Child-Pugh class C).

2.6 Dosage Adjustment with Co-administration of Moderate CYP2C8 Inhibitors

When co-administered with moderate CYP2C8 inhibitors (e.g., clopidogrel, deferasirox and teriflunomide), reduce the dosing of UPTRAVI to once daily [see Drug Interactions (7.1) and Clinical Pharmacology (12.3)] .

3 DOSAGE FORMS AND STRENGTHS

UPTRAVI is available in the following presentations:

Film-Coated Tablets

- 200 mcg selexipag [Light yellow tablet debossed with 2]
- 400 mcg selexipag [Red tablet debossed with 4]
- 600 mcg selexipag [Light violet tablet debossed with 6]
- 800 mcg selexipag [Green tablet debossed with 8]
- 1000 mcg selexipag [Orange tablet debossed with 10]
- 1200 mcg selexipag [Dark violet tablet debossed with 12]
- 1400 mcg selexipag [Dark yellow tablet debossed with 14]
- 1600 mcg selexipag [Brown tablet debossed with 16]

UPTRAVI for Injection

- 1800 mcg selexipag [Lyophilized powder white to almost white broken cake or powdered material, supplied in a 10 mL single-dose glass vial]

4 CONTRAINDICATIONS

Hypersensitivity to the active substance or to any of the excipients.

Concomitant use of strong inhibitors of CYP2C8 (e.g., gemfibrozil) [see Drug Interactions (7.1) and Clinical Pharmacology (12.3)] .

5 WARNINGS AND PRECAUTIONS

5.1 Pulmonary Edema with Pulmonary Veno-Occlusive Disease

Should signs of pulmonary edema occur, consider the possibility of associated pulmonary veno-occlusive disease. If confirmed, discontinue UPTRAVI.

6 ADVERSE REACTIONS

6.1 Clinical Trial Experience

Because clinical trials are conducted under widely varying conditions, adverse reaction rates observed in the clinical trials of a drug cannot be directly compared to rates in the clinical trials of another drug and may not reflect the rates observed in practice.

UPTRAVI Tablets

The safety of UPTRAVI tablets has been evaluated in a long-term, placebo-controlled study enrolling 1,156 patients with symptomatic PAH (GRIPHON study) [see Clinical Studies (14)] . The exposure to UPTRAVI in this trial was up to 4.2 years with median duration of exposure of 1.4 years.

Table 2 presents adverse reactions more frequent on UPTRAVI tablets than on placebo by ≥3%.

Table 2: Adverse Reactions
 | UPTRAVI | Placebo
Adverse Reaction | N=575 | N=577
Headache | 65% | 32%
Diarrhea | 42% | 18%
Jaw pain | 26% | 6%
Nausea | 33% | 18%
Myalgia | 16% | 6%
Vomiting | 18% | 9%
Pain in extremity | 17% | 8%
Flushing | 12% | 5%
Arthralgia | 11% | 8%
Anemia | 8% | 5%
Decreased appetite | 6% | 3%
Rash | 11% | 8%

These adverse reactions are more frequent during the dose titration phase.

Hyperthyroidism was observed in 1% (n=8) of patients on UPTRAVI tablets and in none of the patients on placebo.

UPTRAVI for Injection

Infusion-site reactions (infusion site erythema/redness, pain and swelling) were reported with UPTRAVI for Injection.

Laboratory Test Abnormalities

Hemoglobin

In a Phase 3 placebo-controlled study in patients with PAH, mean absolute changes in hemoglobin at regular visits compared to baseline ranged from −0.34 to −0.02 g/dL in the UPTRAVI group compared to −0.05 to 0.25 g/dL in the placebo group. A decrease in hemoglobin concentration to below 10 g/dL was reported in 8.6% of patients treated with UPTRAVI tablets and 5.0% of placebo-treated patients.

Thyroid Function Tests

In a Phase 3 placebo-controlled study in patients with PAH, a reduction (up to −0.3 MU/L from a baseline median of 2.5 MU/L) in median thyroid-stimulating hormone (TSH) was observed at most visits in the UPTRAVI group. In the placebo group, little change in median values was apparent. There were no mean changes in triiodothyronine or thyroxine in either group.

6.2 Postmarketing Experience

The following adverse reactions have been identified during post approval use of UPTRAVI.

Because these reactions are reported voluntarily from a population of uncertain size, it is not always possible to reliably estimate their frequency or establish a causal relationship to drug exposure.

Vascular disorders: symptomatic hypotension

7 DRUG INTERACTIONS

7.1 CYP2C8 Inhibitors

Concomitant administration with gemfibrozil, a strong inhibitor of CYP2C8, doubled the exposure to selexipag and increased exposure to the active metabolite by approximately 11-fold. Concomitant administration of UPTRAVI with strong inhibitors of CYP2C8 (e.g., gemfibrozil) is contraindicated [see Contraindications (4) and Clinical Pharmacology (12.3)] .

Concomitant administration of UPTRAVI tablets with clopidogrel, a moderate inhibitor of CYP2C8, had no relevant effect on the exposure to selexipag and increased the exposure to the active metabolite by approximately 2.7-fold [see Clinical Pharmacology (12.3)] . Reduce the dosing of UPTRAVI to once daily in patients on a moderate CYP2C8 inhibitor [see Dosage and Administration (2.6)] .

7.2 CYP2C8 Inducers

Concomitant administration with an inducer of CYP2C8 and UGT 1A3 and 2B7 enzymes (rifampin) halved exposure to the active metabolite. Increase dose up to twice of UPTRAVI when co-administered with rifampin. Reduce UPTRAVI when rifampin is stopped [see Clinical Pharmacology (12.3)] .

8 USE IN SPECIFIC POPULATIONS

8.1 Pregnancy

Risk Summary

There are no adequate and well-controlled studies with UPTRAVI in pregnant women. Animal reproduction studies performed with selexipag showed no clinically relevant effects on embryofetal development and survival. A slight reduction in maternal as well as in fetal body weight was observed when pregnant rats were administered selexipag during organogenesis at a dose producing an exposure to the active metabolite approximately 47 times that in humans at the maximum recommended human dose. No adverse developmental outcomes were observed with oral administration of selexipag to pregnant rabbits during organogenesis at exposures to the active metabolite up to 50 times the human exposure at the maximum recommended human dose.

The estimated background risk of major birth defects and miscarriage for the indicated population is unknown. In the U.S. general population, the estimated background risk of major birth defects and miscarriage in clinically recognized pregnancies is 2–4% and 15–20%, respectively.

Data

Animal Data

Pregnant rats were treated with selexipag using oral doses of 2, 6, and 20 mg/kg/day (up to 47 times the exposure to the active metabolite at the maximum recommended human oral dose of 1600 mcg twice daily on an area under the curve [AUC] basis) during the period of organogenesis (gestation days 7 to 17). Selexipag did not cause adverse developmental effects to the fetus in this study. A slight reduction in fetal body weight was observed in parallel with a slight reduction in maternal body weight at the high dose.

Pregnant rabbits were treated with selexipag using oral doses of 3, 10, and 30 mg/kg (up to 50 times the exposure to the active metabolite at the maximum recommended human oral dose of 1600 mcg twice daily on an AUC basis) during the period of organogenesis (gestation days 6 to 18). Selexipag did not cause adverse developmental effects to the fetus in this study.

In a pre- and post-natal development study, pregnant rats were treated with selexipag from gestation day 7 through lactation day 20 at oral doses of 2, 6, and 20 mg/kg/day (up to 35 times the exposure to the active metabolite at the maximum recommended human dose of 1600 mcg twice daily on an AUC basis). Treatment with selexipag did not cause adverse developmental effects in this study at any dose.

8.2 Lactation

It is not known if UPTRAVI is present in human milk. Selexipag or its metabolites were present in the milk of rats. Because many drugs are present in the human milk and because of the potential for serious adverse reactions in nursing infants, discontinue nursing or discontinue UPTRAVI.

8.4 Pediatric Use

Safety and effectiveness in pediatric patients have not been established.

8.5 Geriatric Use

Of the 1,368 subjects in clinical studies of UPTRAVI tablets, 248 subjects were 65 years of age and older, while 19 were 75 and older. No overall differences were observed between these subjects and younger subjects, and other reported clinical experience has not identified differences in responses between the elderly and younger patients, but greater sensitivity cannot be ruled out.

8.6 Patients with Hepatic Impairment

No adjustment to the dosing regimen is needed in patients with mild hepatic impairment (Child-Pugh class A).

A once-daily regimen is recommended in patients with moderate hepatic impairment (Child-Pugh class B) due to the increased exposure to selexipag and its active metabolite. There is no experience with UPTRAVI in patients with severe hepatic impairment (Child-Pugh class C). Avoid use of UPTRAVI in patients with severe hepatic impairment [see Dosage and Administration (2.5) and Clinical Pharmacology (12.3)] .

8.7 Patients with Renal Impairment

No adjustment to the dosing regimen is needed in patients with estimated glomerular filtration rate >15 mL/min/1.73 m^2.

There is no clinical experience with UPTRAVI in patients undergoing dialysis or in patients with glomerular filtration rates <15 mL/min/1.73 m^2 [see Clinical Pharmacology (12.3)] .

10 OVERDOSAGE

Isolated cases of overdose with UPTRAVI tablets up to 3200 mcg were reported. Mild, transient nausea was the only reported consequence. In the event of overdose, supportive measures must be taken as required. Dialysis is unlikely to be effective because selexipag and its active metabolite are highly protein-bound.

11 DESCRIPTION

UPTRAVI contains selexipag, a prostacyclin receptor agonist. The chemical name of selexipag is 2-{4-[(5,6-diphenylpyrazin-2-yl)(isopropyl)amino]butoxy}- N-(methylsulfonyl) acetamide. It has a molecular formula of C26H32N4O4S and a molecular weight of 496.62. Selexipag has the following structural formula:

Selexipag is a pale yellow crystalline powder that is practically insoluble in water. In the solid state selexipag is very stable, is not hygroscopic, and is not light sensitive.

UPTRAVI® (selexipag) tablets: depending on the dose strength, each round film-coated tablet for oral administration contains 200, 400, 600, 800, 1000, 1200, 1400, or 1600 mcg of selexipag. The tablets include the following inactive ingredients: corn starch, D-mannitol, hydroxypropyl cellulose, low substituted hydroxypropyl cellulose, and magnesium stearate. The tablets are film coated with a coating material containing carnauba wax, hypromellose, propylene glycol, titanium dioxide, along with mixtures of iron oxide black, iron oxide red or iron oxide yellow.

UPTRAVI® (selexipag) for injection: contains 1800 mcg of selexipag per vial. UPTRAVI for injection includes the following inactive ingredients: glycine (180 mg), phosphoric acid (3.53 mg), polysorbate 20 (10.8 mg) and sodium hydroxide (for pH adjustment). UPTRAVI for injection is provided in 10 mL Type I clear glass vials closed by a stopper and tear-off aluminum seal.

12 CLINICAL PHARMACOLOGY

12.1 Mechanism of Action

Selexipag is a prostacyclin receptor (IP receptor) agonist that is structurally distinct from prostacyclin. Selexipag is hydrolyzed by carboxylesterase 1 to yield its active metabolite, which is approximately 37-fold as potent as selexipag. Selexipag and the active metabolite are selective for the IP receptor versus other prostanoid receptors (EP1–4, DP, FP, and TP).

12.2 Pharmacodynamics

Cardiac Electrophysiology

At the maximum tolerated dose of 1600 mcg UPTRAVI tablets twice daily, UPTRAVI does not prolong the QT interval to any clinically relevant extent.

Platelet Aggregation

Both selexipag and its active metabolite caused concentration-dependent inhibition of platelet aggregation in vitro with an IC50 of 5.5 µM and 0.21 µM, respectively. However, at clinically relevant concentrations, there was no effect on platelet aggregation test parameters as seen following multiple-dose administrations of UPTRAVI tablets in healthy subjects from 400 to 1800 mcg twice daily.

Pulmonary Hemodynamics

A Phase 2 clinical study assessed hemodynamic variables after 17 weeks of oral treatment in patients with PAH WHO Functional Class II–III and concomitantly receiving endothelin receptor antagonists (ERAs) and/or phosphodiesterase type 5 (PDE-5) inhibitors. Patients titrating UPTRAVI tablets to an individually tolerated dose (200 mcg twice daily increments up to 800 mcg twice daily) (N=33) achieved a statistically-significant mean reduction in pulmonary vascular resistance of 30.3% (95% confidence interval [CI] −44.7%, −12.2%) and an increase in cardiac index (median treatment effect) of 0.41 L/min/m^2 (95% CI 0.10, 0.71) compared to placebo (N=10).

Drug Interaction

In a study in healthy subjects, UPTRAVI tablets (400 mcg twice a day) did not influence the pharmacodynamic effect of warfarin on the international normalized ratio.

12.3 Pharmacokinetics

The pharmacokinetics of selexipag and its active metabolite have been studied primarily in healthy subjects. The pharmacokinetics of selexipag and the active metabolite, after both single- and multiple-dose oral administration, were dose-proportional up to a single dose of 800 mcg and multiple doses of up to 1800 mcg twice daily. The pharmacokinetics of selexipag and the active metabolite, after multiple-dose intravenous administration, were dose-proportional in the tested dose range from 450 to 1800 mcg twice a day.

In healthy subjects, inter-subject variability in exposure (area under the curve over a dosing interval, AUC) at steady-state following oral administration was 43% and 39% for selexipag and the active metabolite, respectively. Intra-subject variability in exposure was 24% and 19% for selexipag and the active metabolite, respectively.

Exposures to selexipag and the active metabolite at steady-state in PAH patients and healthy subjects were similar. The pharmacokinetics of selexipag and the active metabolite in PAH patients were not influenced by the severity of the disease and did not change with time.

The corresponding UPTRAVI tablets and UPTRAVI for injection doses (Table 1) provide similar exposure to the active metabolite in PAH patients at steady-state, whereas the exposure to selexipag is approximately twice as high after intravenous administration compared to oral administration.

Both in healthy subjects and PAH patients, after oral administration, exposure at steady-state to the active metabolite is approximately 3- to 4-fold that of selexipag.

Absorption

The absolute bioavailability of orally administered selexipag is approximately 49%. Upon oral administration, maximum observed plasma concentrations of selexipag and its active metabolite are reached within about 1–3 hours and 3–4 hours, respectively.

In the presence of food, the absorption of selexipag was prolonged resulting in a delayed time to peak concentration (Tmax) and ~30% lower peak plasma concentration (Cmax). The exposure to selexipag and the active metabolite (AUC) did not significantly change in the presence of food.

Distribution

The volume of distribution of selexipag at steady-state is 11.7 L.

Selexipag and its active metabolite are highly bound to plasma proteins (approximately 99% in total and to the same extent to albumin and alpha1-acid glycoprotein).

Metabolism

Selexipag is hydrolyzed to its active metabolite, (free carboxylic acid) in the liver and intestine by carboxylesterases. Oxidative metabolism, catalyzed mainly by CYP2C8 and to a smaller extent by CYP3A4, leads to the formation of hydroxylated and dealkylated products. UGT1A3 and UGT2B7 are involved in the glucuronidation of the active metabolite. Except for the active metabolite, none of the circulating metabolites in human plasma exceeds 3% of the total drug-related material.

Elimination

Elimination of selexipag is predominately via metabolism with a mean terminal half-life of 0.8–2.5 hours. The terminal half-life of the active metabolite is 6.2–13.5 hours. Selexipag does not accumulate following twice daily repeat administration. There is minimal accumulation of the active metabolite upon twice daily repeat administration suggesting that the effective half-life is in the range of 3–4 hours. The total body clearance of selexipag is 17.9 L/hour.

Excretion

In a study in healthy subjects with radiolabeled selexipag, approximately 93% of radioactive drug material was eliminated in feces and only 12% in urine. Neither selexipag nor its active metabolite were found in urine.

Specific Populations

No clinically relevant effects of sex, race, age or body weight on the pharmacokinetics of selexipag and its active metabolite have been observed in healthy subjects or PAH patients.

Age

The pharmacokinetic variables (Cmax and AUC) were similar in adult and elderly subjects up to 75 years of age. There was no effect of age on the pharmacokinetics of selexipag and the active metabolite in PAH patients.

Hepatic Impairment

In subjects with mild (Child-Pugh class A) or moderate (Child-Pugh class B) hepatic impairment, exposure to selexipag was 2- and 4-fold that seen in healthy subjects. Exposure to the active metabolite of selexipag remained almost unchanged in subjects with mild hepatic impairment and was doubled in subjects with moderate hepatic impairment [see Use in Specific Populations (8.6)] .

Based on pharmacokinetic modeling of data from a study in subjects with hepatic impairment, the exposure to the active metabolite at steady-state in subjects with moderate hepatic impairment (Child-Pugh class B) after a once daily regimen is expected to be similar to that in healthy subjects receiving a twice daily regimen. The exposure to selexipag at steady-state in these patients during a once daily regimen is predicted to be approximately 2-fold that seen in healthy subjects receiving a twice-daily regimen.

Renal Impairment

A 40–70% increase in exposure (maximum plasma concentration and area under the plasma concentration-time curve) to selexipag and its active metabolite was observed in subjects with severe renal impairment (estimated glomerular filtration rate ≥15 mL/min/1.73 m^2 and <30 mL/min/1.73 m^2) [see Use in Specific Populations (8.7)] .

Drug Interaction Studies

Drug interaction studies have been performed in adult subjects using UPTRAVI tablets.

In Vitro Studies

Selexipag is hydrolyzed to its active metabolite by carboxylesterases. Selexipag and its active metabolite both undergo oxidative metabolism mainly by CYP2C8 and to a smaller extent by CYP3A4. The glucuronidation of the active metabolite is catalyzed by UGT1A3 and UGT2B7. Selexipag and its active metabolite are substrates of OATP1B1 and OATP1B3. Selexipag is a substrate of P-gp, and the active metabolite is a substrate of the transporter of breast cancer resistance protein (BCRP).

Selexipag and its active metabolite do not inhibit or induce cytochrome P450 enzymes and transport proteins at clinically relevant concentrations.

The results of in vivo drug interaction studies are presented in Figure 1 and 2.

Figure 1 Effect of Other Drugs on Selexipag and its Active Metabolite

* ERA and PDE-5 inhibitor data from GRIPHON.

Figure 2 Effect of UPTRAVI on Other Drugs

13 NONCLINICAL TOXICOLOGY

13.1 Carcinogenesis, Mutagenesis, Impairment of Fertility

Carcinogenesis: In the 2-year carcinogenicity studies, chronic oral administration of selexipag revealed no evidence of carcinogenic potential in rats at 100 mg/kg/day and mice at 500 mg/kg/day which resulted in the exposures to the active metabolite more than 25 times the human exposure at the maximum recommended human oral dose of 1600 mcg twice daily on an AUC basis.

Mutagenesis: Selexipag and the active metabolite are not genotoxic on the basis of the overall evidence of conducted genotoxicity studies.

Fertility: In rats administered with selexipag orally, the no effect dose for effects on fertility was 60 mg/kg/day which resulted in the exposure to the active metabolite approximately 175 times the human exposure at the maximum recommended human oral dose of 1600 mcg twice daily on an AUC basis.

14 CLINICAL STUDIES

14.1 Efficacy of UPTRAVI Tablets in Patients with Pulmonary Arterial Hypertension

The effect of UPTRAVI tablets on progression of PAH was demonstrated in a multi-center, double-blind, placebo-controlled, parallel group, event-driven study (GRIPHON) in 1,156 patients with symptomatic (WHO Functional Class I [0.8%], II [46%], III [53%], and IV [1%]) PAH. Patients were randomized to either placebo (N=582), or UPTRAVI tablets (N=574). The dose was increased in weekly intervals by increments of 200 mcg twice a day to the highest tolerated dose up to 1600 mcg twice a day.

The primary study endpoint was the time to first occurrence up to end-of-treatment of: a) death, b) hospitalization for PAH, c) PAH worsening resulting in need for lung transplantation, or balloon atrial septostomy, d) initiation of parenteral prostanoid therapy or chronic oxygen therapy, or e) other disease progression based on a 15% decrease from baseline in 6MWD plus worsening of Functional Class or need for additional PAH-specific therapy.

The mean age was 48 years, the majority of patients were white (65%) and female (80%). Nearly all patients were in WHO Functional Class II and III at baseline.

Idiopathic or heritable PAH was the most common etiology in the study population (58%) followed by PAH associated with connective tissue disease (29%), PAH associated with congenital heart disease with repaired shunts (10%), drugs and toxins (2%), and HIV (1%).

At baseline, the majority of enrolled patients (80%) were being treated with a stable dose of an endothelin receptor antagonist (15%), a PDE-5 inhibitor (32%), or both (33%).

Patients on UPTRAVI tablets achieved doses within the following groups: 200–400 mcg (23%), 600–1000 mcg (31%) and 1200–1600 mcg (43%).

Treatment with UPTRAVI tablets resulted in a 40% reduction (99% CI: 22 to 54%; two-sided log-rank p-value <0.0001) of the occurrence of primary endpoint events compared to placebo (Table 3; Figure 3). The beneficial effect of UPTRAVI was primarily attributable to a reduction in hospitalization for PAH and a reduction in other disease progression events (Table 3). The observed benefit of UPTRAVI was similar regardless of the dose achieved when patients were titrated to their highest tolerated dose [see Dosage and Administration (2.1)] .

Figure 3 Kaplan-Meier Estimates of the First Morbidity-Mortality Event in GRIPHON

Table 3: Primary Endpoints and Related Components in GRIPHON
 | UPTRAVI N=574 |  | Placebo N=582 |  | Hazard Ratio (99% CI) | p-value
 | n | % | n | %
Primary endpoint events up to the end of treatment
All primary endpoint events As first event: | 155 | 27.0 | 242 | 41.6 | 0.60 [0.46, 0.78] | <0.0001
- Hospitalization for PAH | 78 | 13.6 | 109 | 18.7
- Other disease progression (Decrease in 6MWD plus worsening functional class or need for other therapy) | 38 | 6.6 | 100 | 17.2
- Death | 28 | 4.9 | 18 | 3.1
- Parenteral prostanoid or chronic oxygen therapy | 10 | 1.7 | 13 | 2.2
- PAH worsening resulting in need for lung transplantation or balloon atrial septostomy | 1 | 0.2 | 2 | 0.3

It is not known if the excess number of deaths in the UPTRAVI group is drug-related because there were so few deaths and the imbalance was not observed until 18 months into GRIPHON.

Figures 4A, B, and C show time to first event analyses for primary endpoint components of hospitalization for PAH (A), other disease progression (B), and death (C) all censored 7 days after any primary end point event (because many patients on placebo transitioned to open-label UPTRAVI at this point).

Figure 4A Hospitalization for PAH as the First Endpoint in GRIPHON

Figure 4B Disease Progression as the First Endpoint in GRIPHON

Figure 4C Death as the First Endpoint in GRIPHON

The treatment effect of UPTRAVI on time to first primary event was consistent irrespective of background PAH therapy (i.e., in combination with an ERA, PDE-5i, both, or without background therapy) (Figure 5).

Figure 5 Subgroup Analyses of the Primary Endpoint in GRIPHON

Note: Race group "Other" is not displayed in analysis, as the population is less than 30. EU = Number of UPTRAVI patients with events, NU = Number of patients randomized to UPTRAVI, EP = Number of Placebo patients with events, NP = Number of patients randomized to Placebo, HR = Hazard Ratio, CI = Confidence Interval, the size of the squares represent the number of patients in the subgroup.

Note: The figure above presents effects in various subgroups all of which are baseline characteristics and all were pre-specified. The 99% confidence limits that are shown do not take into account how many comparisons were made, nor do they reflect the effect of a particular factor after adjustment for all other factors. Apparent homogeneity or heterogeneity among groups should not be over-interpreted.

6-Minute Walk Distance (6MWD)

Exercise capacity was evaluated as a secondary endpoint. Median absolute change from baseline to week 26 in 6MWD measured at trough (i.e., at approximately 12 hours post-dose) was +4 meters with UPTRAVI and -9 meters in the placebo group. This resulted in a placebo-corrected median treatment effect of 12 meters (99% CI: 1, 24 meters; two-sided p = 0.005).

Long-Term Treatment of PAH

In long-term follow-up of patients who were treated with UPTRAVI in the pivotal study and the open-label extension (N=574), Kaplan-Meier estimates of survival of these patients across the GRIPHON study and the long-term extension study at 1, 2, 5 and 7 years were 92%, 85%, 71%, and 63%, respectively. The median exposure to UPTRAVI was 3 years. These uncontrolled observations do not allow comparison with a control group not given UPTRAVI and cannot be used to determine the long-term effect of UPTRAVI on mortality.

16 HOW SUPPLIED/STORAGE AND HANDLING

UPTRAVI® (selexipag) film-coated, round tablets are supplied in the following configurations:

Strength (mcg) | Color | Debossing | NDC-XXX Bottle of 60 | NDC-XXX Bottle of 140
200 | Light yellow | 2 | 66215-602-06 | 66215-602-14
400 | Red | 4 | 66215-604-06 | Not Available
600 | Light violet | 6 | 66215-606-06 | Not Available
800 | Green | 8 | 66215-608-06 | Not Available
1000 | Orange | 10 | 66215-610-06 | Not Available
1200 | Dark violet | 12 | 66215-612-06 | Not Available
1400 | Dark yellow | 14 | 66215-614-06 | Not Available
1600 | Brown | 16 | 66215-616-06 | Not Available

UPTRAVI® (selexipag) tablets are also supplied in a Titration Pack [NDC 66215-628-20] that includes a 140-count bottle of 200-mcg tablets and a 60-count bottle of 800-mcg tablets.

STORAGE AND HANDLING

Store at 20°C to 25°C (68°F to 77°F). Excursions are permitted between 15°C and 30°C (59°F and 86°F) [see USP Controlled Room Temperature].

Keep out of reach of children.

UPTRAVI® (selexipag) for injection, for intravenous use, is supplied in a 10 mL Type I glass vial closed by a stopper and sealed with an aluminum flip-off button, containing 1800 mcg of selexipag [NDC 66215-718-01].

UPTRAVI (selexipag) for injection is available in cartons containing 1 single-dose vial.

Storage conditions for UPTRAVI for injection: Store the original carton containing glass vial in a refrigerator at 2°C to 8°C (36ºF to 46ºF) until use in order to protect from light.

17 PATIENT COUNSELING INFORMATION

Advise the patient to read the FDA-approved patient labeling (Patient Information).

Inform Patients:

- To take a missed dose as soon as possible, unless the next dose is within the next 6 hours.
- Not to split, crush, or chew tablets.

Manufactured for:

Actelion Pharmaceuticals US, Inc.
a Janssen Pharmaceutical Company
Titusville, NJ 08560, USA

JN20220728

For patent information: www.janssenpatents.com

© 2015 – 2021 Actelion Pharmaceuticals US, Inc.

PATIENT INFORMATION

UPTRAVI® (up-TRA-vee)
(selexipag)
tablets

UPTRAVI® (up-TRA-vee)
(selexipag)
for injection

What is UPTRAVI?

- UPTRAVI is a prescription medicine used to treat pulmonary arterial hypertension (PAH) which is high blood pressure in the arteries of your lungs.
- UPTRAVI can help slow down the progression of your disease and lower your risk of being hospitalized for PAH.

It is not known if UPTRAVI is safe and effective in children.

Do not take UPTRAVI if you:

- take gemfibrozil because this medicine may affect how UPTRAVI works and cause side effects.
- are allergic to selexipag or any of the other ingredients of this medicine (listed under Inactive ingredients).

Before you take UPTRAVI, tell your healthcare provider about all of your medical conditions, including if you:

- have liver problems.
- have narrowing of the pulmonary veins, a condition called pulmonary veno-occlusive disease.
- are pregnant or plan to become pregnant. It is not known if UPTRAVI will harm your unborn baby.
- are breastfeeding or plan to breastfeed. It is not known if UPTRAVI passes into your breast milk. You and your healthcare provider should decide if you will take UPTRAVI or breastfeed. You should not do both.

Tell your healthcare provider about all the medicines you take, including prescription and over-the-counter medicines, vitamins, and herbal supplements. UPTRAVI and other medicines may affect each other causing side effects. Do not start any new medicine until you check with your healthcare provider.

How should I take UPTRAVI?
UPTRAVI tablets

- Take UPTRAVI exactly as your healthcare provider tells you to take it. Do not stop taking UPTRAVI unless your healthcare provider tells you to stop.
- Your healthcare provider will slowly increase your dose to find the dose of UPTRAVI that is right for you.
- If you have side effects, your healthcare provider may tell you to change your dose of UPTRAVI.
- UPTRAVI can be taken with or without food. Taking UPTRAVI with food may help you tolerate UPTRAVI better.
- UPTRAVI is usually taken 2 times each day.
- Swallow UPTRAVI tablets whole. Do not split, crush or chew UPTRAVI tablets.
- If you miss a dose of UPTRAVI, take it as soon as you remember. If your next scheduled dose is due within 6 hours, skip the missed dose. Take the next dose at your regular time.
- If you miss 3 or more days of UPTRAVI, call your healthcare provider to see if your dose needs to be changed.
- If you take too much UPTRAVI, call your healthcare provider or go to the nearest hospital emergency room right away.

UPTRAVI given by intravenous (IV) injection

- Your healthcare provider will give you UPTRAVI into your vein through an intravenous (IV) line.
- Your healthcare provider will decide how much UPTRAVI for injection you will receive each day, based on your current dose of UPTRAVI tablets.

What are the possible side effects of UPTRAVI?
The most common side effects of UPTRAVI include:

- headache
- jaw pain
- muscle pain
- pain in arms or legs
- pain in joints
- decreased appetite
- diarrhea

- nausea
- vomiting
- flushing
- low red blood cell count
- rash
- pain, redness or swelling at the injection site for UPTRAVI for injection

These are not all of the possible side effects of UPTRAVI.
Call your doctor for medical advice about side effects. You may report side effects to FDA at 1-800-FDA-1088.

How should I store UPTRAVI tablets?
Store UPTRAVI tablets at room temperature between 68°F and 77°F (20°C and 25°C).
Keep UPTRAVI and all medicines out of the reach of children.

General information about the safe and effective use of UPTRAVI
Medicines are sometimes prescribed for purposes other than those listed in a Patient Information leaflet. Do not use UPTRAVI for a condition for which it was not prescribed. Do not give UPTRAVI to other people, even if they have the same symptoms that you have. It may harm them. You can ask your healthcare provider or pharmacist for information about UPTRAVI that is written for health professionals.

What are the ingredients in UPTRAVI?
UPTRAVI tablets
Active ingredient: selexipag
Inactive ingredients: corn starch, D-mannitol, hydroxypropyl cellulose, low substituted hydroxypropyl cellulose, and magnesium stearate. The tablets are film coated with a coating material containing carnauba wax, hypromellose, propylene glycol, titanium dioxide, along with mixtures of iron oxide black, iron oxide red, or iron oxide yellow.
UPTRAVI for injection
Active ingredient: selexipag
Inactive ingredients: glycine, phosphoric acid, polysorbate 20, and sodium hydroxide.
Manufactured for:
Actelion Pharmaceuticals US, Inc.
a Janssen Pharmaceutical Company
Titusville, NJ 08560, USA
JN20220728
For patent information: www.janssenpatents.com
© 2015 – 2021 Actelion Pharmaceuticals US, Inc.
For more information, contact Janssen at 1-800-526-7736 (1-800-JANSSEN) or go to www.UPTRAVI.com.

This Patient Information has been approved by the U.S. Food and Drug Administration.

Revised: 07/2022

PRINCIPAL DISPLAY PANEL - 200 mcg Tablet Bottle Carton

NDC 66215-602-06

Uptravi®
(selexipag)
tablets

200 mcg

Rx only

60 film-coated
tablets

janssen

PRINCIPAL DISPLAY PANEL - 400 mcg Tablet Bottle Carton

NDC 66215-604-06

Uptravi®
(selexipag)
tablets

400 mcg

Rx only

60 film-coated
tablets

janssen

PRINCIPAL DISPLAY PANEL - 600 mcg Tablet Bottle Carton

NDC 66215-606-06

Uptravi®
(selexipag)
tablets

600 mcg

Rx only

60 film-coated
tablets

janssen

PRINCIPAL DISPLAY PANEL - 800 mcg Tablet Bottle Carton

NDC 66215-608-06

Uptravi®
(selexipag)
tablets

800 mcg

Rx only

60 film-coated
tablets

janssen

PRINCIPAL DISPLAY PANEL - 1000 mcg Tablet Bottle Carton

NDC 66215-610-06

Uptravi®
(selexipag)
tablets

1000 mcg

Rx only

60 film-coated
tablets

janssen

PRINCIPAL DISPLAY PANEL - 1200 mcg Tablet Bottle Carton

NDC 66215-612-06

Uptravi®
(selexipag)
tablets

1200 mcg

Rx only

60 film-coated
tablets

janssen

PRINCIPAL DISPLAY PANEL - 1400 mcg Tablet Bottle Carton

NDC 66215-614-06

Uptravi®
(selexipag)
tablets

1400 mcg

Rx only

60 film-coated
tablets

janssen

PRINCIPAL DISPLAY PANEL - 1600 mcg Tablet Bottle Carton

NDC 66215-616-06

Uptravi®
(selexipag)
tablets

1600 mcg

Rx only

60 film-coated
tablets

janssen

PRINCIPAL DISPLAY PANEL - Kit Carton

NDC 66215-628-20

TITRATION PACK

Uptravi®
(selexipag)
tablets

200 mcg

Rx only

140 film-coated
tablets

Uptravi®
(selexipag)
tablets

800 mcg

Rx only

60 film-coated
tablets

janssen

PRINCIPAL DISPLAY PANEL - 1,800 mcg Vial Carton

NDC 66215-718-01

Uptravi®
(selexipag)
for injection

1,800 mcg/vial

FOR INTRAVENOUS INFUSION ONLY
Reconstitute and Dilute Prior to Use.

Single-dose vial. Discard unused portion.

Rx only
Sterile

One Vial

OPEN
HERE